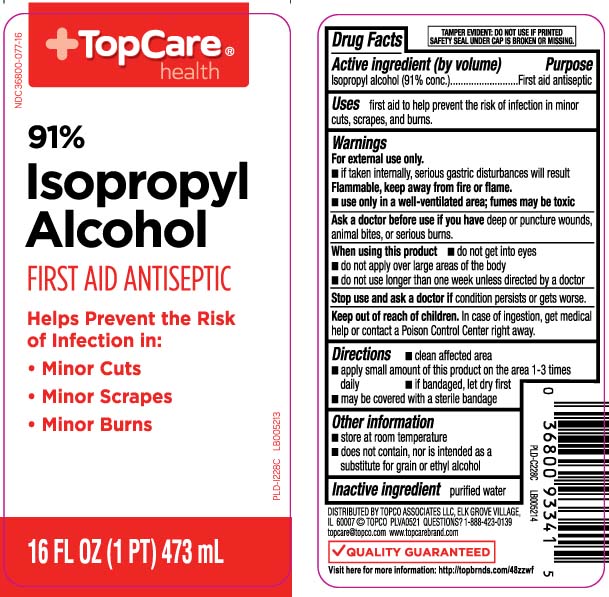 DRUG LABEL: Isopropyl Alcohol
NDC: 36800-077 | Form: LIQUID
Manufacturer: TOP CARE (Topco Associates LLC)
Category: otc | Type: HUMAN OTC DRUG LABEL
Date: 20250409

ACTIVE INGREDIENTS: ISOPROPYL ALCOHOL 91 mL/100 mL
INACTIVE INGREDIENTS: WATER

Drug Facts

Active ingredient (by volume)

Isopropyl alcohol (91% conc.)

Purpose

first aid antiseptic

Uses

first aid to help prevent the risk of infection in minor cuts, scrapes and burns

Warnings

For external use only.

- if taken internally serious gastric disturbances will result

Flammable, keep away from fire or flame.

- use only in a well-ventilated area; fumes may be toxic

Ask a doctor before use if you have

deep or puncture wounds, animal bites or serious burns

When using this product

- do not get into eyes
- do not apply over large areas of the body
- do not use longer than one week unless directed by a doctor

Stop use and ask a doctor if

condition persists or gets worse

Keep out of reach of children.

In case of ingestion, get medical help or contact a Poison Control Center right away.

Directions

- clean affected area
- apply small amount of this product on the area 1-3 times daily
- if bandaged, let dry first
- may be covered with a sterile bandage

Other information

- store at room temperature
- does not contain, nor is intended as a substitute for grain or ethyl alcohol

Inactive ingredient

purified water

Principal Display Panel

91% Isopropyl Alcohol

FIRST AID ANTISEPTIC

Helps prevent the risk of infection in:

- Minor cuts
- Minor scrapes
- Minor burns

FL OZ (mL)

Question? 1-888-423-0139

TAMPER EVIDENT: DO NOT USE IF PRINTED SAFETY SEAL UNDER THE CAP IS BROKEN OR MISSING.

DISTRIBUTED BY TOPCO ASSOCIATES LLC

ELK GROVE VILLAGE, IL 60007

topcare@topco.com

Package Label

TOPCARE HEALTH 91% Isopropyl Alcohol